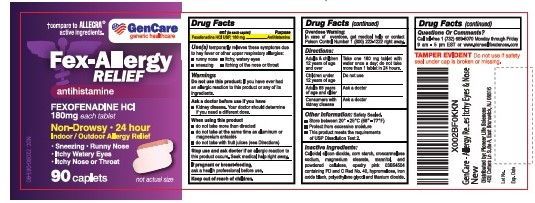 DRUG LABEL: Fex-Allergy Relief
NDC: 72090-061 | Form: TABLET
Manufacturer: Pioneer Life Sciences, LLC
Category: otc | Type: HUMAN OTC DRUG LABEL
Date: 20200929

ACTIVE INGREDIENTS: FEXOFENADINE HYDROCHLORIDE 180 mg/1 1
INACTIVE INGREDIENTS: MANNITOL; STARCH, CORN; SILICON DIOXIDE; CROSCARMELLOSE SODIUM; HYPROMELLOSE, UNSPECIFIED; MAGNESIUM STEARATE; POLYETHYLENE GLYCOL, UNSPECIFIED; CELLULOSE, MICROCRYSTALLINE; TITANIUM DIOXIDE; FD&C RED NO. 40

Fex-Allergy relief

Active Ingredient

Fexofenadine hydrochloride USP, 180 mg

Purpose

Antihistamine

Uses:

- temporarily relieves these symptoms due to hay fever or other upper respiratory allergies:
- runny nose
- sneezing
- itchy, watery eyes
- itching of the nose or throat

Do not use:

if you have ever had an allergic reaction to this product or any of its ingredients.

WHEN USING THIS PRODUCT

- do not take more than directed
- do not take at the same time as aluminum or magnesium antacids
- do not take with fruit juices (see Directions)

ASK A DOCTOR BEFORE USE IF

Kidney disease. Your doctor should determine if you need a different dose.

STOP USE AND ASK A DOCTOR IF

an allergic reaction to this product occurs. Seek medical help right away.

If pregnant or breast-feeding, ask a health professional before use.

KEEP OUT OF REACH OF CHILDREN

In case of overdose, get medical help or contact a Poison Control Center right away.

DIRECTIONS

adults and children 12 years of age and over | Take one 180 mg tablet with water once a day; do not take more than 1 tablets in 24 hours.
children under 12 years of age | do not use
adults 65 years of age and older | ask a doctor
consumers with kidney disease | ask a doctor

OTHER INFORMATION

- store at 20°-25°C (68°-77°F)
- protect from excessive moisture
- this product meets the requirement of USP dissolution test 2.

INACTIVE INGREDIENTS

colloidal silicon dioxide, corn starch,croscarmellose sodium, magnesium stearate,mannitol and microcrystalline cellulose, opadry pink 03B54504 containing FD and C red No.40, iron oxide black,hypromellose,polyethylene glycol, titanium dioxide.

QUESTIONS OR COMMENTS?

Call 1-732-698-5070 Monday through Friday 9AM–5PM EST or www.pioneerlifesciences.com

Keep out of reach of children.

In case of overdose, get medical help or contact a Poison Control Center (1-800-222-1222) right away.